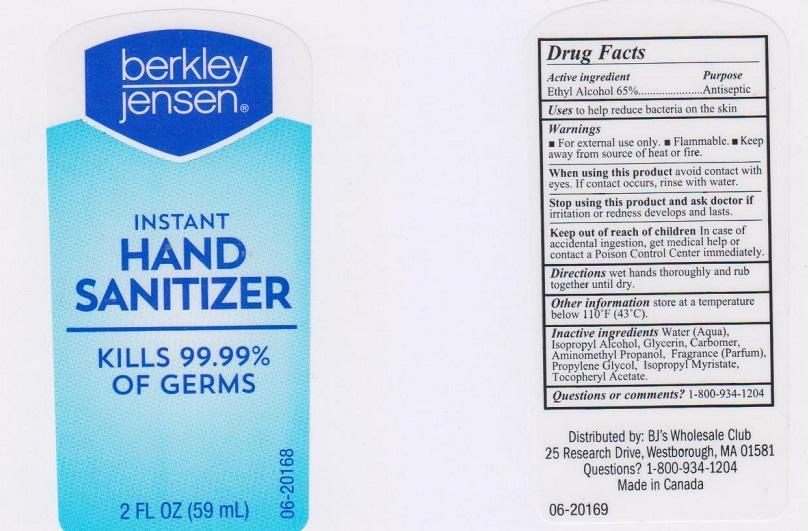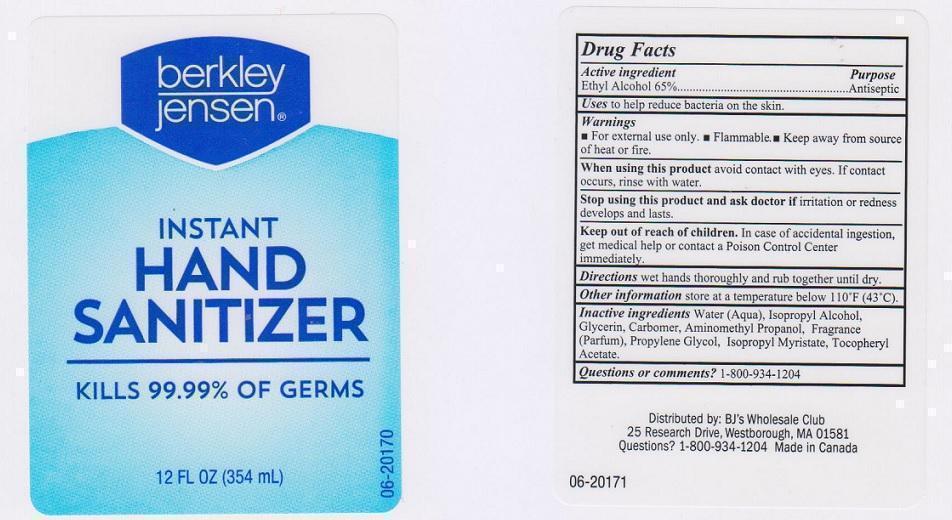 DRUG LABEL: BERKLEY JENSEN
NDC: 68391-167 | Form: LIQUID
Manufacturer: BJWC
Category: otc | Type: HUMAN OTC DRUG LABEL
Date: 20150114

ACTIVE INGREDIENTS: ALCOHOL 650 mg/1 mL
INACTIVE INGREDIENTS: WATER; ISOPROPYL ALCOHOL; GLYCERIN; CARBOMER 934; AMINOMETHYLPROPANOL; PROPYLENE GLYCOL; ISOPROPYL MYRISTATE; .ALPHA.-TOCOPHEROL ACETATE

DRUG FACTS

ACTIVE INGREDIENT

ETHYL ALCOHOL 65%

PURPOSE

ANTISEPTIC

USES

TO HELP REDUCE BACTERIA ON THE SKIN

WARNINGS

- FOR EXTERNAL USE ONLY
- FLAMMABLE
- KEEP AWAY FROM SOURCE OF HEAT OR FIRE

WHEN USING THIS PRODUCT

AVOID CONTACT WITH EYES. IF CONTACT OCCURS, RINSE WITH WATER

STOP USING THIS PRODUCT AND ASK DOCTOR IF

IRRITATION OR REDNESS DEVELOPS AND LASTS

KEEP OUT OF REACH OF CHILDREN

IN CASE OF ACCIDENTAL INGESTION, GET MEDICAL HELP OR CONTACT A POISON CONTROL CENTER IMMEDIATELY

DIRECTIONS

WET HANDS THOROUGHLY AND RUB TOGETHER UNTIL DRY

OTHER INFORMATION

STORE AT A TEMPERATURE BELOW 110°F (43°C)

INACTIVE INGREDIENTS

WATER (AQUA), ISOPROPYL ALCOHOL, GLYCERIN, CARBOMER, AMINOMETHYL PROPANOL, FRAGRANCE (PARFUM), PROPYLENE GLYCOL, ISOPROPYL MYRISTATE, TOCOPHERYL ACETATE

QUESTIONS OR COMMENTS?

1-800-934-1204